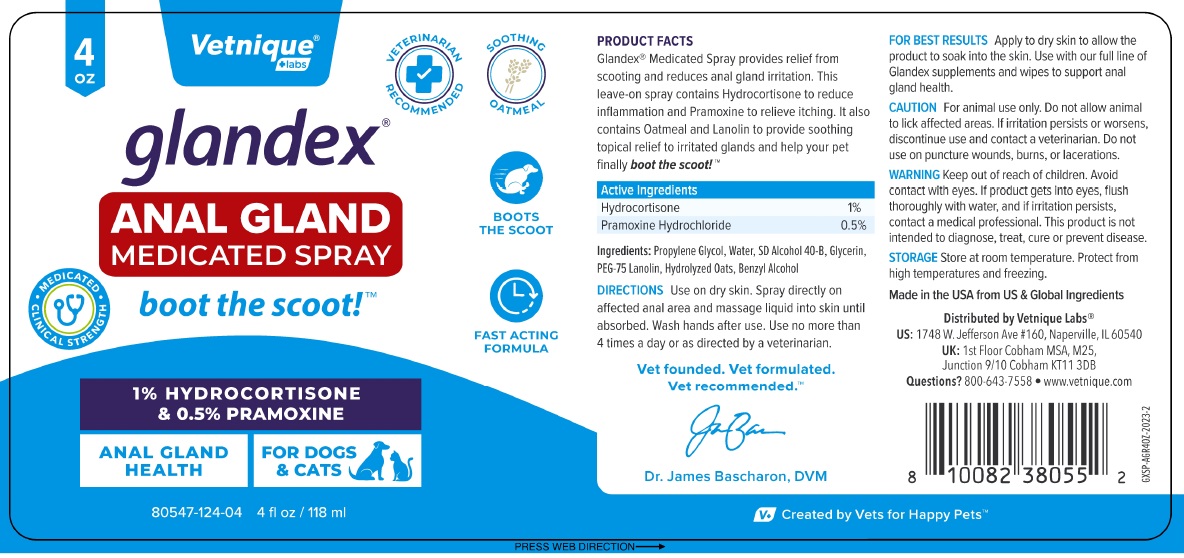 DRUG LABEL: glandex ANAL GLAND MEDICATED
NDC: 80547-124 | Form: SPRAY
Manufacturer: Vetnique Labs Llc
Category: animal | Type: OTC ANIMAL DRUG LABEL
Date: 20231212

ACTIVE INGREDIENTS: HYDROCORTISONE 10 mg/1 mL; PRAMOXINE HYDROCHLORIDE 5 mg/1 mL
INACTIVE INGREDIENTS: PROPYLENE GLYCOL; WATER; ALCOHOL; GLYCERIN; PEG-75 LANOLIN; OAT; BENZYL ALCOHOL

glandex® ANAL GLAND MEDICATED SPRAY

PRODUCT FACTS

Glandex® Medicated Spray provides relief from scooting and reduces anal gland irritation. This leave-on spray contains Hydrocortisone to reduce inflammation and Pramoxine to relieve itching. It also contains Oatmeal and Lanolin to provide soothing topical relief to irritated glands and help your pet finally boot the scoot!™

Active Ingredients

Hydrocortisone 1%
Pramoxine Hydrochloride 0.5%

Ingredients:

Propylene Glycol, Water, SD Alcohol 40-B, Glycerin, PEG-75 Lanolin, Hydrolyzed Oats, Benzyl Alcohol

DIRECTIONS

Use on dry skin. Spray directly on affected anal area and massage liquid into skin until absorbed. Wash hands after use. Use no more than 4 times a day, or as directed by a veterinarian.

FOR BEST RESULTS Apply to dry skin to allow the product to soak into the skin. Use with our full line of Glandex supplements and wipes to support anal gland health.

CAUTION

For animal use only. Do not allow animal to lick affected areas. If irritation persists or worsens, discontinue use and contact a veterinarian. Do not use on puncture wounds, burns, or lacerations.

WARNING

Keep out of reach of children. Avoid contact with eyes. If product gets into eyes, flush thoroughly with water, and if irritation persists, contact a medical professional. This product is not intended to diagnose, treat, cure, or prevent disease.

STORAGE

Store at room temperature. Protect from high temperatures and freezing.

VETERINARIAN RECOMMENDED

SOOTHING OATMEAL

MEDICATED CLINICAL STRENGTH

ANAL GLAND HEALTH

FOR DOGS & CATS

FAST ACTING FORMULA

Vet founded. Vet formulated.
Vet recommended.™

Made in the USA from US & Global Ingredients

Distributed by Vetnique Labs®

US: 1748 W. Jefferson Ave #160, Naperville, IL 60540

UK: 1st Floor Cobham MSA, M25,
Junction 9/10 Cobham KT11 3DB

Questions? 800-643-7558 • www.vetnique.com

V+ Created by Vets for Happy Pets™